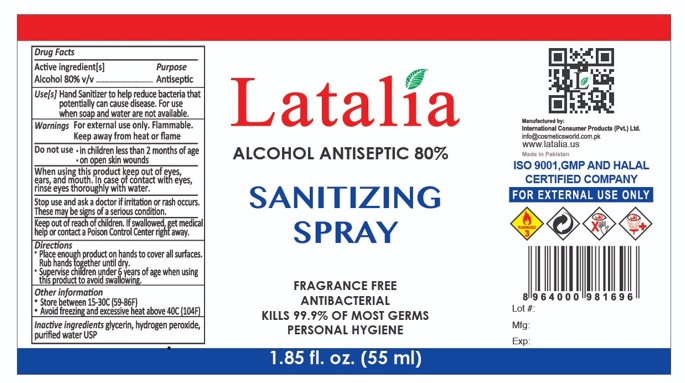 DRUG LABEL: Latalia Alcohol Antiseptic 80% Sanitizing
NDC: 80016-005 | Form: LIQUID
Manufacturer: INTERNATIONAL CONSUMER PRODUCTS (PVT) LTD
Category: otc | Type: HUMAN OTC DRUG LABEL
Date: 20260203

ACTIVE INGREDIENTS: ALCOHOL 80 mL/100 mL
INACTIVE INGREDIENTS: GLYCERIN; HYDROGEN PEROXIDE; WATER

Latalia Alcohol Antiseptic 80% Sanitizing Spray

Active ingredient[s]

Alcohol 80% v/v

Purpose

Antiseptic

Use[s]

Hand Sanitizer to help reduce bacteria that potentially can cause disease. For use when soap and water are not available.

Warnings

For external use only. Flammable.
Keep away from heat or flame

Do not use

- in children less than 2 months of age
- on open skin wounds

When using this product

keep out of eyes, ears, and mouth. In case of contact with eyes, rinse eyes thoroughly with water.

Stop use and ask a doctor

if irritation or rash occurs. These may be signs of a serious condition.

Keep out of reach of children.

If swallowed, get medical help or contact a Poison control Center right away.

Directions

- Place enough product on hands to cover all surfaces.
- Rub hands together until dry.
- Supervise children under 6 years of age when using this product to avoid swallowing.

Other information

- Store between 15-30C (59-86F)
- Avoid freezing and excessive heat above 40C (104F)

Inactive ingredients

glycerin, hydrogen peroxide, purified water USP